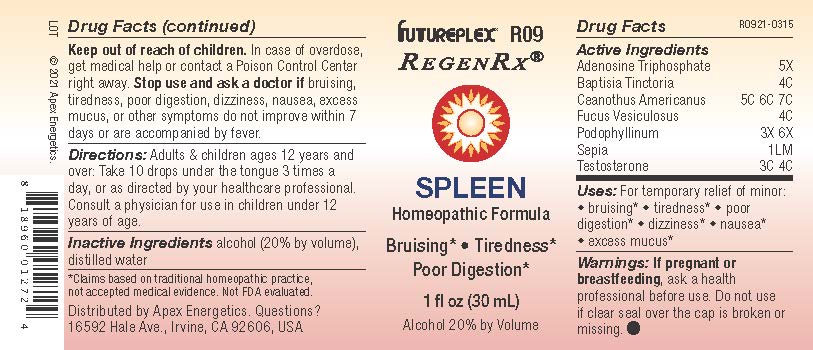 DRUG LABEL: R09
NDC: 63479-1809 | Form: SOLUTION/ DROPS
Manufacturer: Apex Energetics Inc.
Category: homeopathic | Type: HUMAN OTC DRUG LABEL
Date: 20240108
DEA Schedule: CIII

ACTIVE INGREDIENTS: TESTOSTERONE 4 [hp_C]/1 mL; ADENOSINE TRIPHOSPHATE 5 [hp_X]/1 mL; BAPTISIA TINCTORIA ROOT 4 [hp_C]/1 mL; PODOPHYLLUM RESIN 6 [hp_X]/1 mL; CEANOTHUS AMERICANUS LEAF 7 [hp_C]/1 mL; FUCUS VESICULOSUS 4 [hp_C]/1 mL; SEPIA OFFICINALIS JUICE 1 [hp_Q]/1 mL
INACTIVE INGREDIENTS: ALCOHOL; WATER

R09

Active Ingredients
Adenosine Triphosphate | 5X
Baptisia Tinctoria | 4C
Ceanothus Americanus | 5C 6C 7C
Fucus Vesiculosus | 4C
Podophyllinum | 3X 6X
Sepia | 1LM
Testosterone | 3C 4C

INDICATIONS AND USAGE

Uses:

For temporary relief of minor:

bruising*

tiredness*

poor digestion*

dizziness*

nausea*

excess mucus*

*Claims based on traditional homeopathic practice, not accepted medical evidence. Not FDA evaluated.

Warnings:

PREGNANCY OR BREAST FEEDING

If pregnant or breastfeeding, ask a health professional before use.

Do not use if clear seal over the cap is broken or missing.

Keep out of reach of children. In case of overdose, get medical help or contact a Poison Control Center right away.

Stop use and ask a doctor if bruising, tiredness, poor digestion, dizziness, nausea, excess mucus, or other symptoms do not improve within 7 days or are accompanied by fever.

Directions:

Adults & children ages 12 years and over: Take 10 drops under the tongue 3 times a day, or as directed by your healthcare professional. Consult a physician for use in children under 12 years of age.

Inactive Ingredients

alcohol (20% by volume), distilled water

Distributed by Apex Energetics. Questions?

16592 Hale Ave., Irvine, CA 92606, USA

PACKAGE LABEL

FUTUREPLEX® R09

REGENRX®

SPLEEN

Homeopathic Formula

Bruising*

Tiredness*

Poor Digestion*

1 fl oz (30 mL)

Alcohol 20% by Volume